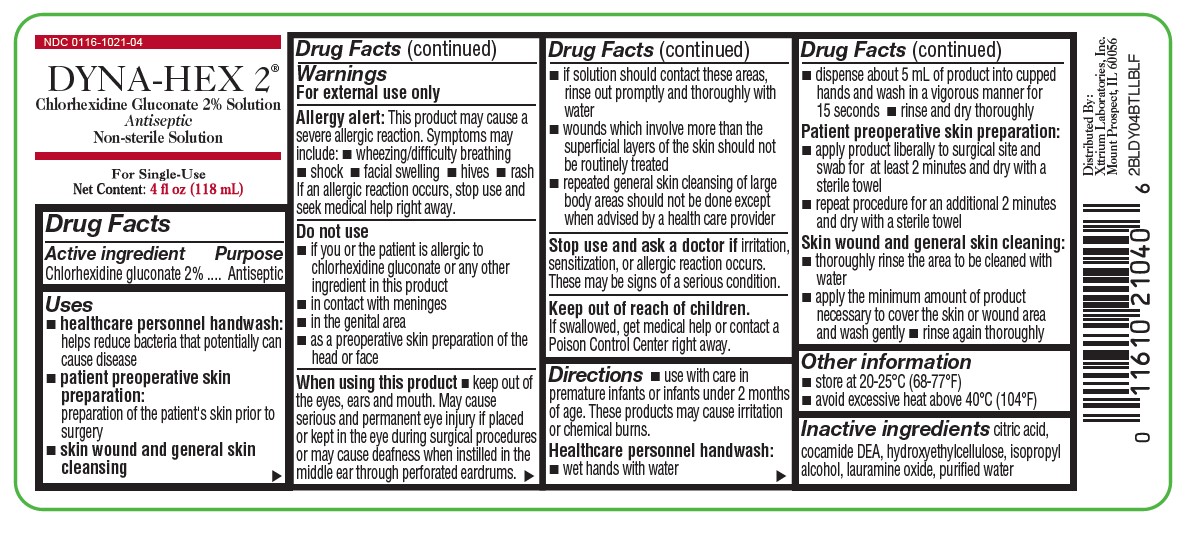 DRUG LABEL: DYNA-HEX
NDC: 0116-1021 | Form: LIQUID
Manufacturer: Xttrium Laboratories, Inc.
Category: otc | Type: HUMAN OTC DRUG LABEL
Date: 20250430

ACTIVE INGREDIENTS: CHLORHEXIDINE GLUCONATE 2 g/100 mL
INACTIVE INGREDIENTS: HYDROXYETHYL CELLULOSE (2000 MPA.S AT 1%); ISOPROPYL ALCOHOL; CITRIC ACID MONOHYDRATE; COCO DIETHANOLAMIDE; LAURAMINE OXIDE; WATER

4-oz Dyna-Hex 2

Drug Facts

Active ingredient

Chlorhexidine Gluconate 2% Solution

Purpose

Antiseptic

Uses

- healthcare personnel handwash: helps reduce bacteria that potentially can cause disease
- patient preoperative skin preparation: preparation of the patient's skin prior to surgery
- skin wound and skin cleansing

Warnings

For external use only

Allergy alert:

This product may cause a severe allergic reaction. Symptoms may include:

- wheezing/difficulty breathing
- shock
- facial swelling
- hives
- rash

if an allergic reaction occurs, stop use and seek medical help right awau

Do not use

- if you or the patient is allergic to chlorhexidine gluconate or any other ingredient in this product
- in contact with meninges
- in the genital area
- as a preoperative skin preparation of the head or face

When using this product

- keep out of eyes, ears, and mouth. May cause serious and permenent eye injury if placed or kept in the eye during surgical procedures or may cause deafness when instilled in the middle ear through perforated eardrums.
- if solution should contact these areas, rinse out promptly and thoroughly with water
- wounds which involve more than the superficial layers of the skin should not be routinely treated
- repeated general skin cleansing of large body areas should not be done except when advised by a health care provider

Stop use and ask a doctor if

irritation, sensitization, or allergic reaction occurs. These may be signs of a serious condition.

Keep out of reach of children

If swallowed, get medical help or contact a Poison Control Center right away

Directions

- use with care in premature infants under 2 months of age. These products may cause irritation or chemical burns.

Healthcare personnel handwash:

- wet hands with water
- dispense about 5 mL of product into cupped hands and wash in a vigorous manner for 15 seconds
- rinse and dry thoroughly

Patient preoperative skin preparation:

- apply product liberally to surgical site and swab for at least 2 minutes and dry with a sterile towel
- repeat procedurefor an additional 2 minuted and dry with a sterile towel

Skin wound and general skin cleaning:

- thoroughly rinse the area to be cleaned with water
- appl the minimum amount of product necessary to cover the skin or wound area and wash gently
- rinse again thoroughly

Other information

- store at 20-25ºC (68-77ºF)
- avoid excessive heat above 40ºC (104ºF)

Inactive ingredients

citric acid, cocamide DEA, hydroxyethylcellulose, isopropyl alcohol, lauramine oxide, purified water

Questions or comments?

call 1-800-587-3721

Monday through Friday 8:00 AM to 4:30 PM CST

RECENT MAJOR CHANGES

Directions and Uses updated

PACKAGE LABEL

NDA 0116-1021-04

DYNA-HEX 2 ®

(Chlorhexidine Gluconate 2% Solution)

Antiseptic

Contains: 2% Chlorhexidine Gluconate

FOR EXTERNAL USE ONLY

For single-use

Net Contents: 4 fl oz (118 mL)

Distributed By:
Xttrium Laboratories, Inc.
Mount Prospect, IL 60056
2BLDY04BTLLBLF